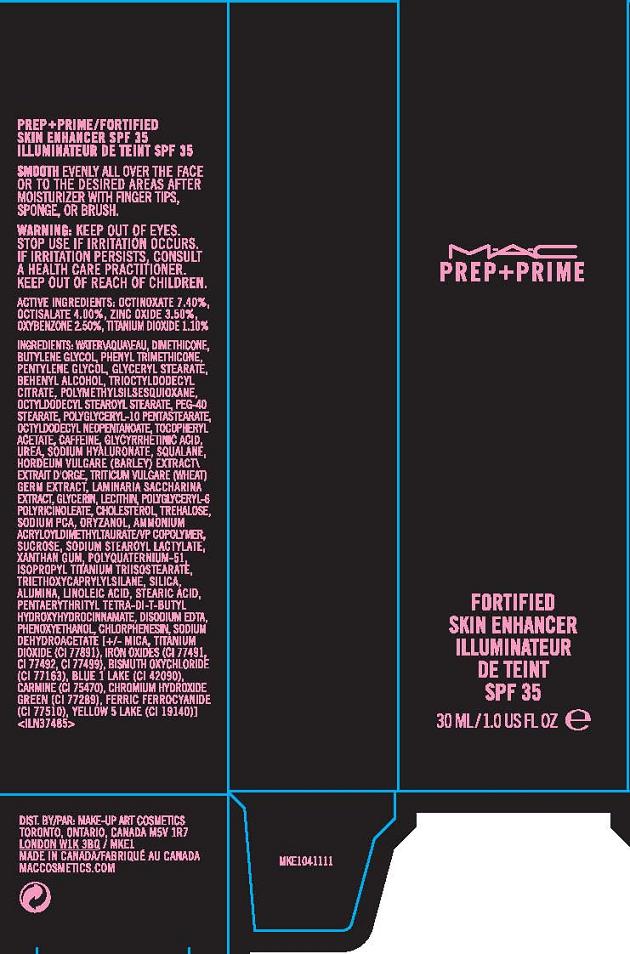 DRUG LABEL: PREP AND PRIME
NDC: 40046-0039 | Form: CREAM
Manufacturer: MAKEUP ART COSMETICS
Category: otc | Type: HUMAN OTC DRUG LABEL
Date: 20110714

ACTIVE INGREDIENTS: OCTINOXATE 7.4 mL/100 mL; OCTISALATE 4.0 mL/100 mL; ZINC OXIDE 3.5 mL/100 mL; OXYBENZONE 2.5 mL/100 mL; TITANIUM DIOXIDE 1.1 mL/100 mL
INACTIVE INGREDIENTS: WATER; DIMETHICONE; BUTYLENE GLYCOL; PHENYL TRIMETHICONE; PENTYLENE GLYCOL; GLYCERYL MONOSTEARATE; DOCOSANOL; POLYMETHYLSILSESQUIOXANE (11 MICRONS); OCTYLDODECYL STEAROYL STEARATE; PEG-40 STEARATE; OCTYLDODECYL NEOPENTANOATE; ALPHA-TOCOPHEROL ACETATE; CAFFEINE; ENOXOLONE; UREA; HYALURONATE SODIUM; SQUALANE; BARLEY; WHEAT GERM; GLYCERIN; LECITHIN, SOYBEAN; CHOLESTEROL; TREHALOSE; SODIUM PYRROLIDONE CARBOXYLATE; GAMMA ORYZANOL; SUCROSE; SODIUM STEAROYL LACTYLATE; XANTHAN GUM; TRIETHOXYCAPRYLYLSILANE; SILICON DIOXIDE; ALUMINUM OXIDE; LINOLEIC ACID; STEARIC ACID; PENTAERYTHRITOL TETRAKIS(3-(3,5-DI-TERT-BUTYL-4-HYDROXYPHENYL)PROPIONATE); EDETATE DISODIUM; PHENOXYETHANOL; CHLORPHENESIN; SODIUM DEHYDROACETATE; MICA; FERRIC OXIDE RED; FD&C YELLOW NO. 5

ACTIVE INGREDIENT

ACTIVE INGREDIENTS: OCTINOXATE 7.40% [] OCTISALATE 4.00% [] ZINC OXIDE 3.50% [] OXYBENZONE 2.50% [] TITANIUM DIOXIDE 1.10%

INACTIVE INGREDIENT

INACTIVE INGREDIENTS: WATER\AQUA\EAU [] DIMETHICONE [] BUTYLENE GLYCOL [] PHENYL TRIMETHICONE [] PENTYLENE GLYCOL [] GLYCERYL STEARATE [] BEHENYL ALCOHOL [] TRIOCTYLDODECYL CITRATE [] POLYMETHYLSILSESQUIOXANE [] OCTYLDODECYL STEAROYL STEARATE [] PEG-40 STEARATE [] POLYGLYCERYL-10 PENTASTEARATE [] OCTYLDODECYL NEOPENTANOATE [] TOCOPHERYL ACETATE [] CAFFEINE [] GLYCYRRHETINIC ACID [] UREA [] SODIUM HYALURONATE [] SQUALANE [] HORDEUM VULGARE (BARLEY) EXTRACT\EXTRAIT D'ORGE [] TRITICUM VULGARE (WHEAT) GERM EXTRACT [] LAMINARIA SACCHARINA EXTRACT [] GLYCERIN [] LECITHIN [] POLYGLYCERYL-6 POLYRICINOLEATE [] CHOLESTEROL [] TREHALOSE [] SODIUM PCA [] ORYZANOL [] AMMONIUM ACRYLOYLDIMETHYLTAURATE/VP COPOLYMER [] SUCROSE [] SODIUM STEAROYL LACTYLATE [] XANTHAN GUM [] POLYQUATERNIUM-51 [] ISOPROPYL TITANIUM TRIISOSTEARATE [] TRIETHOXYCAPRYLYLSILANE [] SILICA [] ALUMINA [] LINOLEIC ACID [] STEARIC ACID [] PENTAERYTHRITYL TETRA-DI-T-BUTYL HYDROXYHYDROCINNAMATE [] DISODIUM EDTA [] PHENOXYETHANOL [] CHLORPHENESIN [] SODIUM DEHYDROACETATE [] [+/- MICA [] TITANIUM DIOXIDE (CI 77891) [] IRON OXIDES (CI 77491, CI 77492, CI 77499) [] BISMUTH OXYCHLORIDE (CI 77163) [] BLUE 1 LAKE (CI 42090) [] CARMINE (CI 75470) [] CHROMIUM HYDROXIDE GREEN (CI 77289) [] FERRIC FERROCYANIDE (CI 77510) [] YELLOW 5 LAKE (CI 19140)]

WHEN USING

DIRECTIONS: SMOOTH EVENLY ALL OVER THE FACE OR TO THE DESIRED AREAS AFTER MOISTURIZER WITH FINGERTIPS, SPONGE OR BRUSH.

WARNINGS

WARNING: KEEP OUT OF EYES. STOP USE IF IRRITATION OCCURS. IF IRRITATION PERSISTS, DISCONTINUE USE AND CONTACT A HEALTH CARE PRACTITIONER.

KEEP OUT OF REACH OF CHILDREN.

PACKAGE LABEL

PRINCIPAL DISPLAY PANEL:

MAC

PREP + PRIME

FORTIFIED SKIN ENHANCER

SPF 35

NT WT 1.0 FL OZ/ 30 ML

DISTR BY MAKE UP ART COSMETICS

TORONTO, ONTARIO, CANADA M5V 1R7